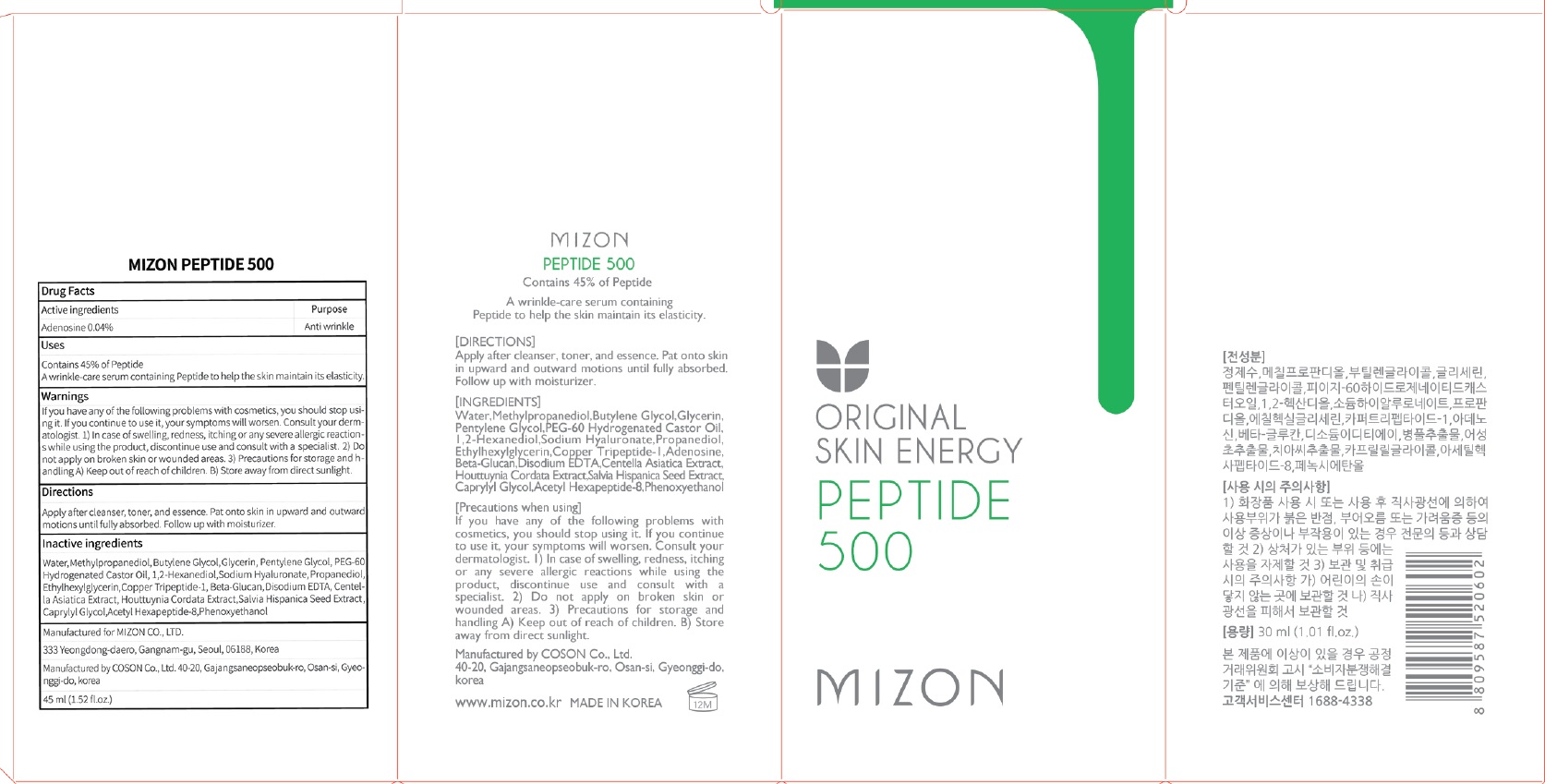 DRUG LABEL: MIZON PEPTIDE 500
NDC: 57718-350 | Form: LIQUID
Manufacturer: MIZON CO.,LTD.
Category: otc | Type: HUMAN OTC DRUG LABEL
Date: 20180726

ACTIVE INGREDIENTS: Adenosine 0.012 g/30 mL
INACTIVE INGREDIENTS: Water; Methylpropanediol

ACTIVE INGREDIENT

Active ingredients: Adenosine 0.04%

INACTIVE INGREDIENT

Inactive ingredients:

Water,Methylpropanediol,Butylene Glycol,Glycerin, Pentylene Glycol,PEG-60 Hydrogenated Castor Oil, 1,2-Hexanediol,Sodium Hyaluronate,Propanediol, Ethylhexylglycerin,Copper Tripeptide-1, Beta-Glucan,Disodium EDTA,Centella Asiatica Extract, Houttuynia Cordata Extract,Salvia Hispanica Seed Extract, Caprylyl Glycol,Acetyl Hexapeptide-8,Phenoxyethanol

PURPOSE

Purpose: Anti wrinkle

WARNINGS

If you have any of the following problems with cosmetics, you should stop using it. If you continue to use it, your symptoms will worsen. Consult your dermatologist. 1) In case of swelling, redness, itching or any severe allergic reactions while using the product, discontinue use and consult with a specialist. 2) Do not apply on broken skin or wounded areas. 3) Precautions for storage and handling A) Keep out of reach of children. B) Store away from direct sunlight.

KEEP OUT OF REACH OF CHILDREN

Uses

Contains 45% of Peptide

A wrinkle-care serum containing Peptide to help the skin maintain its elasticity.

Directions

Apply after cleanser, toner, and essence. Pat onto skin in upward and outward motions until fully absorbed. Follow up with moisturizer.